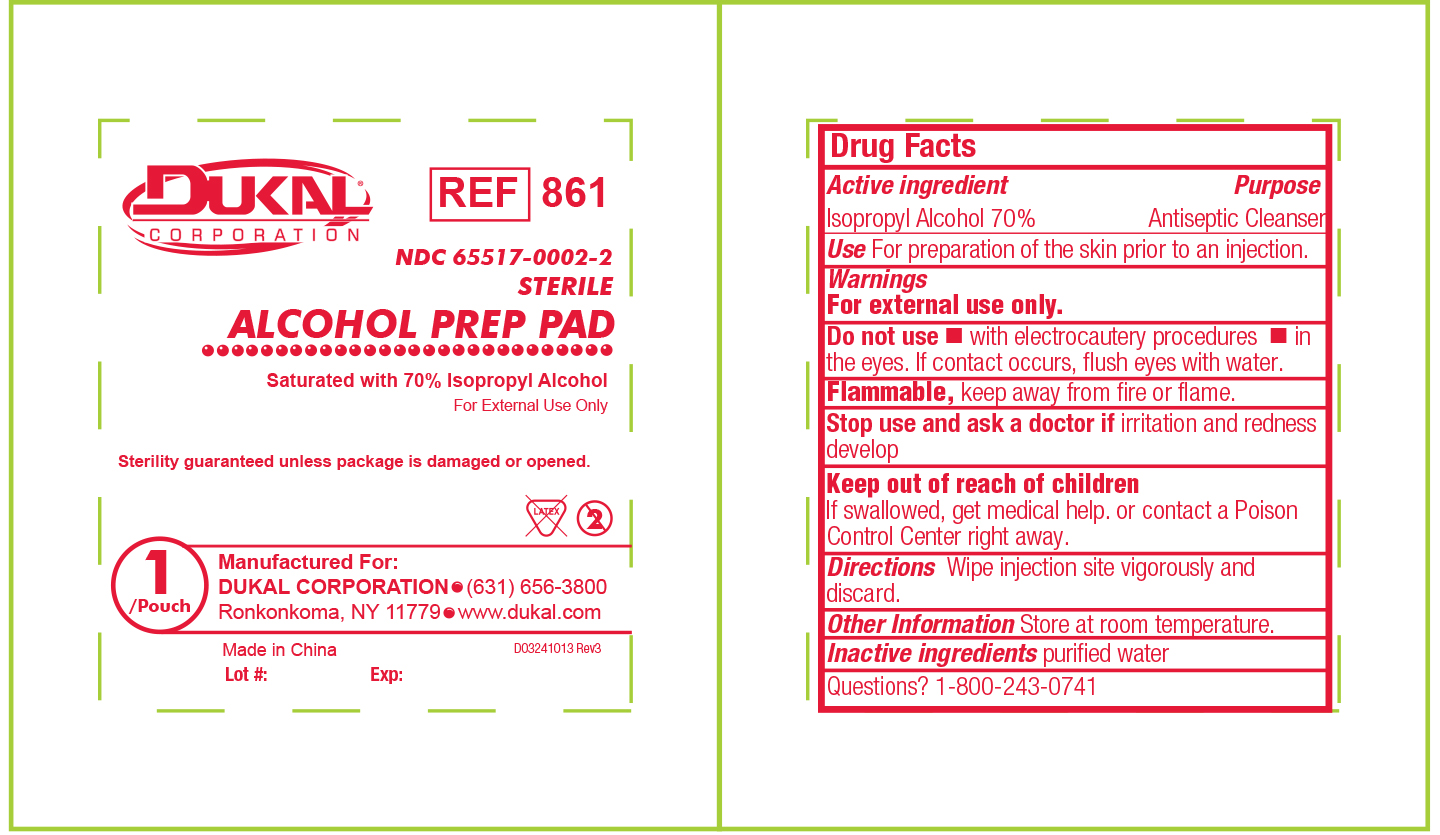 DRUG LABEL: Dukal Sterile Alcohol Prep Pad
NDC: 65517-0002 | Form: SWAB
Manufacturer: Dukal Corporation
Category: otc | Type: HUMAN OTC DRUG LABEL
Date: 20190228

ACTIVE INGREDIENTS: ISOPROPYL ALCOHOL 0.7 mL/1 mL
INACTIVE INGREDIENTS: WATER

Drug Facts

Active Ingredients

Isopropyl Alcohol 70%

Purpose

Antiseptic Cleanser

Use

For Preparation of Skin prior to an injection

Warnings

- For External Use Only
- Flammable, Keep away from fire or flame

Do Not Use

- with electrocautery procedures
- In the Eyes. If contact occurs, flush eyes with water

Stop Use

If irritation and redness develop. If condition persists, consult your health care practitioner.

Keep out of reach of children

If swallowed, get medical help or contact a Poison Control Center right away.

Directions

Wipe injection site vigorously and discard.

Other Information

Store at Room Temperature 15 - 30 C (59 - 86 F)

Inactive Ingredient

purified water

PACKAGE LABEL

Dukal Corporation REF 861

NDC 65517-0002-2

Sterile

ALCOHOL PREP PAD

Saturated with 70% Isopropyl Alcohol

For External Use Only

Sterility guaranteed unless package is damaged or opened.

Latex 2

1 / Pouch

Manufactured For:

Dukal Corporation

Ronkonkoma, NY 11779

631-656-3800 www.dukal.com

Made in China